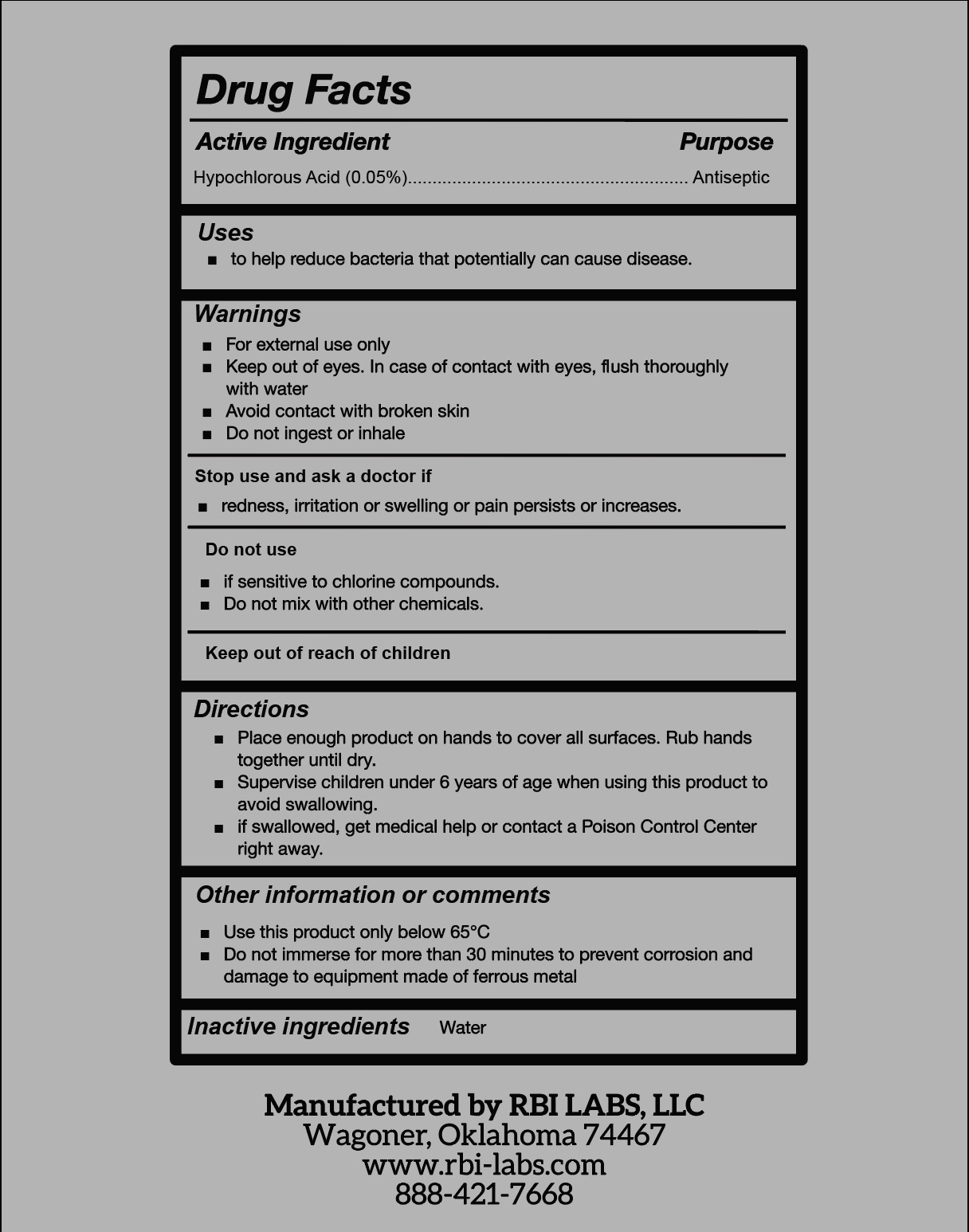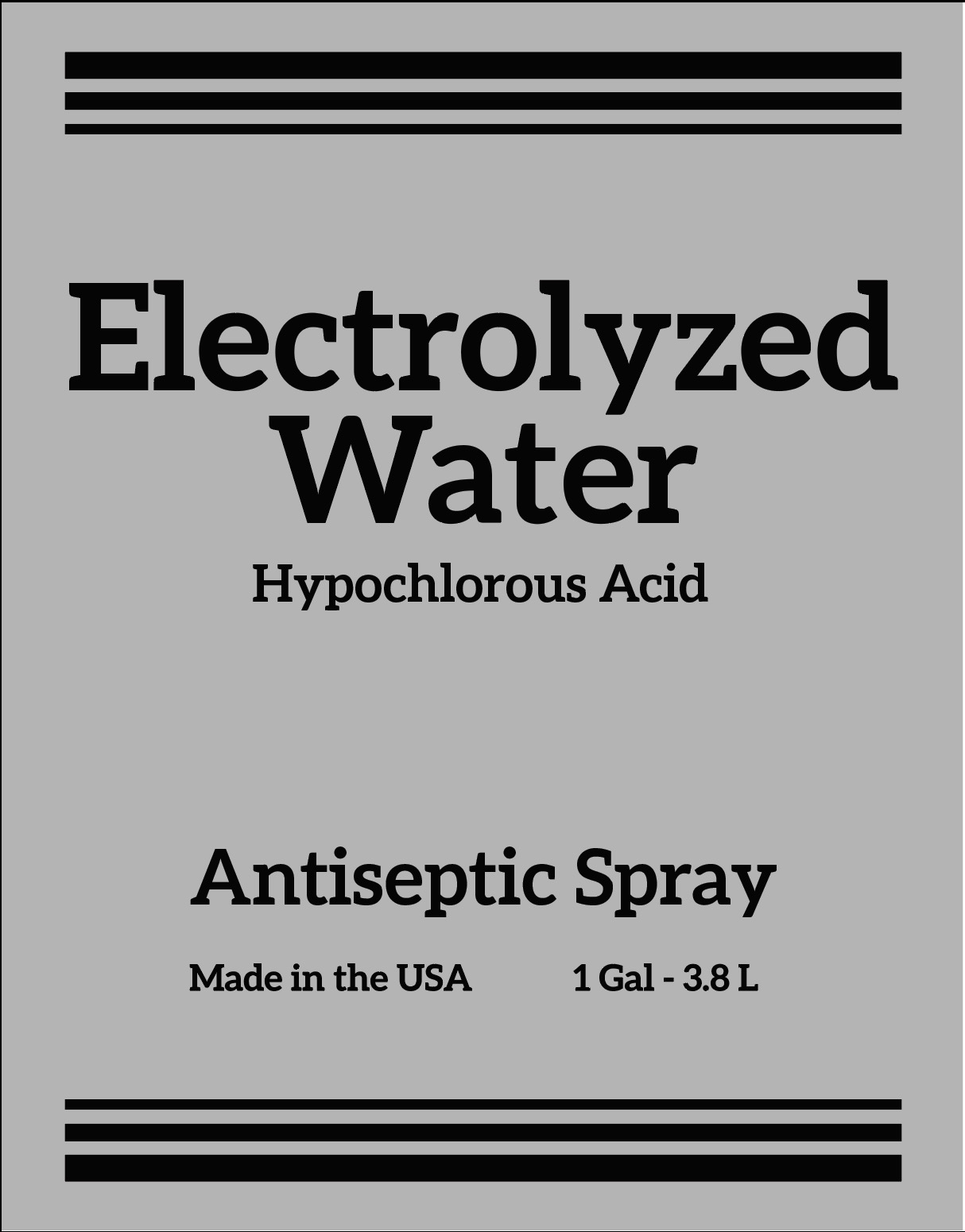 DRUG LABEL: Electrolyzed Water
NDC: 80932-002 | Form: SPRAY
Manufacturer: ROOTS BEAUTY INNOVATIONS LLC
Category: otc | Type: HUMAN OTC DRUG LABEL
Date: 20220201

ACTIVE INGREDIENTS: HYPOCHLOROUS ACID 0.05 g/100 mL
INACTIVE INGREDIENTS: WATER

Electrolyzed Water Hypochlorous Acid

Active Ingredient

Hypochlorous Acid 0.05%

Purpose

Antiseptic

Uses

- to prevent and treat infection of the skin

Warnings

For external use only

Stop use and ask a doctor if

- redness, irritation or swelling or pain persists or increases.

Do not use

- if sensitive to chlorine compounds.
- Do not mix with other chemicals.
- if swallowed, get medical help or contact a Poison Control Center right away.

Keep out of reach of children

Directions

- to use as liquid sterilization by immersing completely for about 3 to 5 minutes.
- For instruments that are difficult to immerse, spray and sterilize for about 3 minutes before wiping off.

Questions and Comments

Use this product only below 65°C

Do not immerse for more than 30 minutes to prevent corrosion and damage to equipment made of ferrous metal

Inactive Ingredient

Water

PACKAGE LABEL

3785 mL NDC:80932-002-37